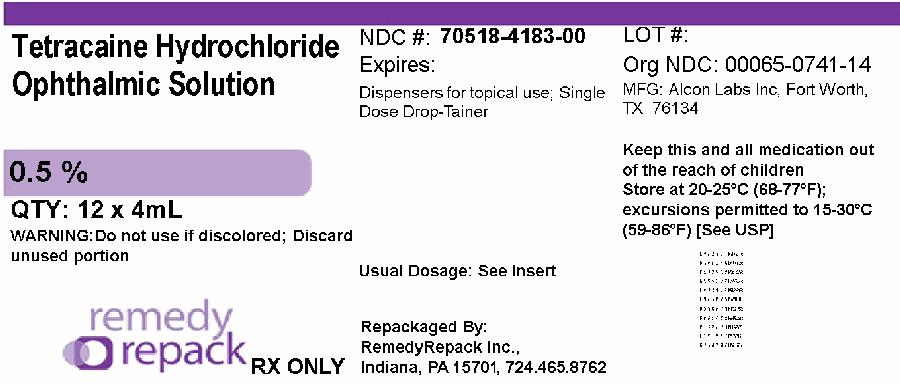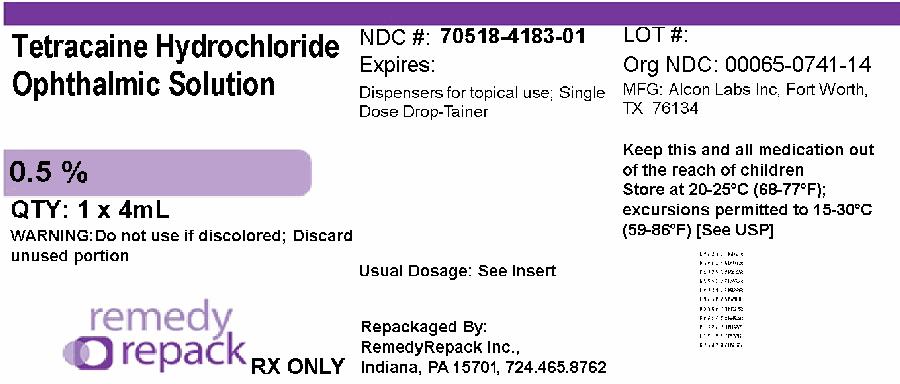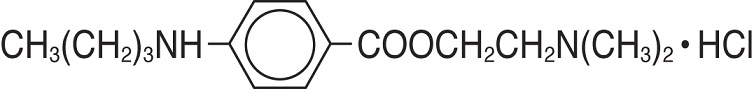 DRUG LABEL: Tetracaine Hydrochloride
NDC: 70518-4183 | Form: SOLUTION
Manufacturer: REMEDYREPACK INC.
Category: prescription | Type: HUMAN PRESCRIPTION DRUG LABEL
Date: 20250522

ACTIVE INGREDIENTS: TETRACAINE HYDROCHLORIDE 5 mg/1 mL
INACTIVE INGREDIENTS: SODIUM CHLORIDE; SODIUM ACETATE; ACETIC ACID; WATER

HIGHLIGHTS OF PRESCRIBING INFORMATION

These highlights do not include all the information needed to use Tetracaine Hydrochloride Ophthalmic Solution 0.5% STERI‑UNIT®safely and effectively. See full prescribing information for Tetracaine Hydrochloride Ophthalmic Solution.
Tetracaine Hydrochloride Ophthalmic Solution 0.5% STERI‑UNIT®,
for topical ophthalmic use
Initial U.S. Approval: 1965

1 INDICATIONS AND USAGE

Tetracaine Hydrochloride Ophthalmic Solution 0.5% is an ester local anesthetic indicated for procedures requiring a rapid and short-acting topical ophthalmic anesthetic. (1)

2 DOSAGE AND ADMINISTRATION

One drop topically in the eye(s) as needed. Discard unused portion. (2.1)

3 DOSAGE FORMS AND STRENGTHS

Sterile ophthalmic solution containing 0.5% tetracaine hydrochloride (3)

4 CONTRAINDICATIONS

None (4)

RECENT MAJOR CHANGES

Warnings and Precautions (5.4) 2/2022

5 WARNINGS AND PRECAUTIONS

- Do not use intracamerally since use may damage corneal endothelial cells (5.1)
- Prolonged use or abuse may lead to corneal epithelial toxicity and may manifest as epithelial defects which may progress to permanent corneal damage. (5.2)
- Patients should not touch the eye for at least 10-20 minutes after using anesthetic as accidental injuries can occur due to insensitivity of the eye. (5.3)
- For Administration by Healthcare Provider:Tetracaine Hydrochloride Ophthalmic Solution 0.5% is not intended for patient self-administration. (5.4)

6 ADVERSE REACTIONS

Ocular adverse events: stinging, burning, conjunctival redness (6)

To report SUSPECTED ADVERSE REACTIONS, contact Alcon Laboratories, Inc., at 1-800-757-9195 or FDA at 1-800-FDA-1088 or www.fda.gov/medwatch.

FULL PRESCRIBING INFORMATION

1 INDICATIONS AND USAGE

Tetracaine Hydrochloride Ophthalmic Solution 0.5% is indicated for procedures requiring a rapid and short-acting topical ophthalmic anesthetic.

2 DOSAGE AND ADMINISTRATION

2.1 Topical Administration

One drop topically in the eye as needed. Discard unused portion.

2.2 Sterile Field Administration

Open package using standard aseptic technique. The DROP‑TAINER®dispenser may then be allowed to fall upon a sterile surface. The entire outer surface of the DROP‑TAINER®dispenser and its contents are sterile.

3 DOSAGE FORMS AND STRENGTHS

Sterile ophthalmic solution containing 0.5% w/v tetracaine hydrochloride equivalent to tetracaine 0.44% w/v.

4 CONTRAINDICATIONS

None.

5 WARNINGS AND PRECAUTIONS

5.1 Corneal injury with Intracameral Use

Not for injection or intraocular use. Do not use intracamerally because use of TetracaineHydrochloride Ophthalmic Solution 0.5% may lead to damage of the corneal endothelial cells.

5.2 Corneal Toxicity

Prolonged use or abuse may lead to corneal epithelial toxicity and may manifest as epithelial defects which may progress to permanent corneal damage.

5.3 Corneal Injury due to Insensitivity

Patients should not touch the eye for at least 10-20 minutes after using anesthetic as accidental injuries can occur due to insensitivity of the eye.

5.4 For Administration by Healthcare Provider

Tetracaine Hydrochloride Ophthalmic Solution 0.5% is indicated for administration under the direct supervision of a healthcare provider. Tetracaine Hydrochloride Ophthalmic Solution 0.5% is not intended for patient self-administration [ see Warnings and Precautions (5.2)].

6 ADVERSE REACTIONS

The following serious ocular adverse reactions are described elsewhere in the labeling:

- Corneal injury with Intracameral Use [See Warnings and Precautions (5.1)]
- Corneal Toxicity [See Warnings and Precautions (5.2)]
- Corneal Injury due to Insensitivity [ See Warnings and Precautions (5.3)]

The following adverse reactions have been identified following use of Tetracaine Hydrochloride Ophthalmic Solution 0.5%. Because these reactions are reported voluntarily from a population of uncertain size, it is not always possible to reliably estimate their frequency or establish a causal relationship to drug exposure.

Ocular Adverse Reactions
Transient stinging, burning, and conjunctival redness, eye irritation, eye pain, ocular discomfort.

8 USE IN SPECIFIC POPULATIONS

8.1 Pregnancy

Risk Summary
There are no adequate and well-controlled studies with Tetracaine Hydrochloride Ophthalmic Solution 0.5% in pregnant women. Animal developmental and reproductive toxicity studies with tetracaine hydrochloride have not been reported in the published literature.

8.2 Lactation

Risk Summary
There are no data to assess whether Tetracaine Hydrochloride Ophthalmic Solution 0.5% is excreted in human milk or to assess its effects on milk production/excretion. The developmental and health benefits of breastfeeding should be considered along with the mother’s clinical need for Tetracaine Hydrochloride Ophthalmic Solution 0.5% and any potential adverse effects on the breastfed child from Tetracaine Hydrochloride Ophthalmic Solution 0.5% or from the underlying maternal condition.

8.3 Females and Males of Reproductive Potential

No human data on the effect of Tetracaine Hydrochloride Ophthalmic Solution 0.5% on fertility are available.

8.4 Pediatric Use

Safety in the pediatric population has been demonstrated in clinical trials. Efficacy of tetracaine hydrochloride ophthalmic solution for use in pediatric patients has been extrapolated from adequate and well controlled clinical trials in the adult population.

8.5 Geriatric Use

No overall differences in safety or effectiveness of tetracaine hydrochloride ophthalmic solution have been observed between elderly and younger patients.

10 OVERDOSAGE

Prolonged use of a topical ocular anesthetic including TetracaineHydrochloride Ophthalmic Solution 0.5% may produce permanent corneal opacification and ulceration with accompanying visual loss. Symptoms related to systemic toxicity consist mainly of effects on the neurologic and cardiovascular systems.

11 DESCRIPTION

Tetracaine hydrochloride is chemically designated as benzoic acid, 4-(butylamino)-,2-(dimethylamino) ethyl ester, monohydrochloride. Its chemical formula is C15H24N2O2• HCl and it is represented by the chemical structure:

Tetracaine hydrochloride is a fine, white, crystalline, odorless powder and has a molecular weight of 300.82. Tetracaine Hydrochloride Ophthalmic Solution 0.5% has a pH of 3.7 to 5.5.

Active ingredient:tetracaine hydrochloride 0.5% w/v (equivalent to 0.44% w/v tetracaine)

Inactive ingredients:sodium chloride, sodium acetate trihydrate, acetic acid (to adjust pH approximately 4.5), Water for Injection, USP

12 CLINICAL PHARMACOLOGY

12.1 Mechanism of Action

Tetracaine blocks sodium ion channels required for the initiation and conduction of neuronal impulses thereby affecting local anesthesia.

12.3 Pharmacokinetics

The systemic exposure to tetracaine following topical ocular administration of Tetracaine Hydrochloride Ophthalmic Solution 0.5% has not been studied. Tetracaine hydrochloride is metabolized by plasma pseudocholinesterases and nonspecific esterases in ocular tissues.

13 NONCLINICAL TOXICOLOGY

13.1 Carcinogenesis, Mutagenesis, Impairment of Fertility

Studies to assess the genotoxicity of tetracaine hydrochloride have not been reported in the published literature. Long-term animal studies have not been conducted to evaluate the carcinogenic potential of tetracaine hydrochloride.

Animal studies to assess the effects of tetracaine hydrochloride on fertility have not been reported in the published literature.

14 CLINICAL STUDIES

Topical administration of tetracainehydrochloride ophthalmic solution results in localized temporary anesthesia. The maximum effect is achieved within 10–20 seconds after instillation, with efficacy lasting 10–20 minutes. Duration of effect can be extended with repeated dosing. [see Corneal toxicity (5.2)and Overdosage (10)] .

16 HOW SUPPLIED/STORAGE AND HANDLING

Tetracaine Hydrochloride Ophthalmic Solution 0.5% STERI-UNITS® is supplied as single patient use, 4 mL filled in 4-mL natural medium- or low-density polyethylene plastic DROP-TAINER® dispensers and natural low-density polyethylene tips with white polypropylene caps in a carton of 12. Each sterilized DROP-TAINER® dispenser is packaged in a clear PVC and Tyvek blister. This product does not contain a preservative; discard unused portion.

NDC: 70518-4183-00

NDC: 70518-4183-01

PACKAGING: 12 in 2 CARTON

PACKAGING: 1-4 mL BOTTLE, DROPPER TYPE 0

Storage: Store at 2°C to 25°C (36°F to 77°F). Protect from light. Do not use if solution contains crystals, is cloudy, or discolored.

Repackaged and Distributed By:

Remedy Repack, Inc.

625 Kolter Dr. Suite #4 Indiana, PA 1-724-465-8762

17 PATIENT COUNSELING INFORMATION

Eye Care Precaution
Advise patients that, due to the effect of the anesthetic, their eyes will be insensitive up to 20 minutes and that care should be taken to avoid accidental injuries.

Repackaged By / Distributed By: RemedyRepack Inc.

625 Kolter Drive, Indiana, PA 15701

(724) 465-8762

PACKAGE LABEL

DRUG: Tetracaine Hydrochloride

GENERIC: tetracaine hydrochloride

DOSAGE: SOLUTION

ADMINSTRATION: OPHTHALMIC

NDC: 70518-4183-0

NDC: 70518-4183-1

PACKAGING: 4 mL in 1 BOTTLE, DROPPER

OUTER PACKAGING: 12 in 1 CARTON

ACTIVE INGREDIENT(S):

- Tetracaine Hydrochloride 5mg in 1mL

INACTIVE INGREDIENT(S):

- Sodium Chloride
- Sodium Acetate
- Acetic Acid
- Water